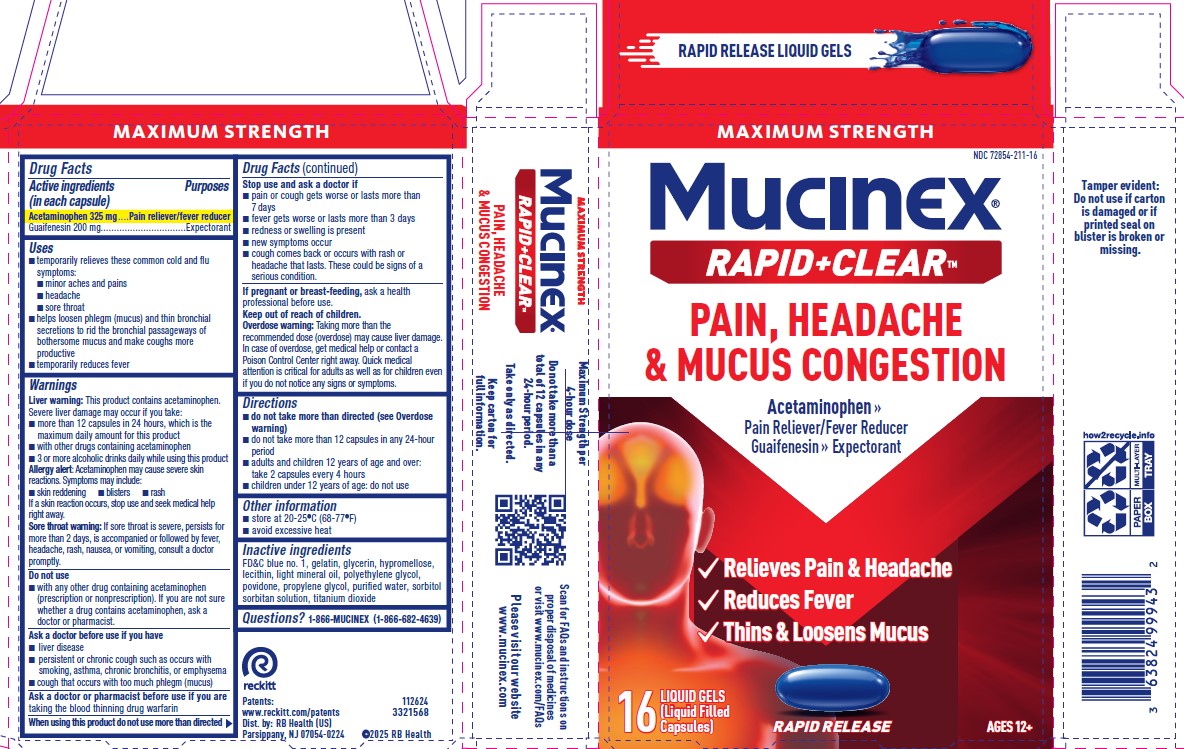 DRUG LABEL: Mucinex Sinus Max Clear and Cool
NDC: 72854-211 | Form: CAPSULE, LIQUID FILLED
Manufacturer: RB Health (US) LLC
Category: otc | Type: HUMAN OTC DRUG LABEL
Date: 20250618

ACTIVE INGREDIENTS: ACETAMINOPHEN 325 mg/1 1; GUAIFENESIN 200 mg/1 1
INACTIVE INGREDIENTS: FD&C BLUE NO. 1; LECITHIN, SOYBEAN; GLYCERIN; SORBITOL SOLUTION; WATER; HYPROMELLOSE, UNSPECIFIED; GELATIN, UNSPECIFIED; PROPYLENE GLYCOL; TITANIUM DIOXIDE; LIGHT MINERAL OIL; POLYETHYLENE GLYCOL, UNSPECIFIED; POVIDONE, UNSPECIFIED

MUCINEX® Rapid Clear® Pain, Headache & Mucus Congestion Liquid Gels

Drug Facts

ACTIVE INGREDIENT

Acetaminophen 325 mg.............Pain reliever/fever reducer
Guaifenesin 200 mg...............................................Expectorant

Uses

■ temporarily relieves these common cold and flu symptoms:
■ minor aches and pains
■ headache ■ sore throat
■ helps loosen phlegm (mucus) and thin bronchial secretions
to rid the bronchial passageways of bothersome mucus
and make coughs more productive
■ temporarily reduces fever

Warnings

Liver warning: This product contains acetaminophen.
Severe liver damage may occur if you take:
■ more than 12 liquid gels in 24 hours, which is the
maximum daily amount
■ with other drugs containing acetaminophen
■ 3 or more alcoholic drinks daily while using this product
Allergy alert: Acetaminophen may cause severe skin
reactions. Symptoms may include:
■ skin reddening ■ blisters ■ rash
If a skin reaction occurs, stop use and seek medical help right
away.
Sore throat warning: If sore throat is severe, persists for
more than 2 days, is accompanied or followed by fever,
headache, rash, nausea, or vomiting, consult a doctor
promptly.

Directions

■ do not take more than directed (see Overdose warning)
■ do not take more than 12 liquid gels in any 24-hour period
■ adults and children 12 years of age and over: take
2 liquid gels every 4 hours
■ children under 12 years of age: do not use

RECENT MAJOR CHANGES

■ do not take more than directed (see Overdose warning)
■ do not take more than 12 liquid gels in any 24-hour period
■ adults and children 12 years of age and over: take
2 liquid gels every 4 hours
■ children under 12 years of age: do not use

Other Information

■ store at 20-25°C (68-77°F)
■ avoid excessive heat

Inactive Ingredients

FD&C blue no. 1, gelatin, glycerin, hypromellose, lecithin, light
mineral oil, polyethylene glycol, povidone, propylene glycol,
purified water, sorbitol sorbitan solution, titanium dioxide

Questions?

1-866-MUCINEX (1-866-682-4639)

Dist. by: RB Health (US)
Parsippany, NJ 07054-0224
©2025 RB Health

Keep out of reach of children.

Principal Display Panel

Fast Dissolving Liquid Gels!

NDC 72854-211

Mucinex®

Acetaminophen – Pain Reliever/Fever Reducer
Guaifenesin – Expectorant

✓Thins & Loosens Mucus
✓Relieves Pain & Headache
✓Reduces Fever

LIQUID GELS
(Liquid Filled Capsules)

Actual Size

DAY TIME
FOR AGES 12+